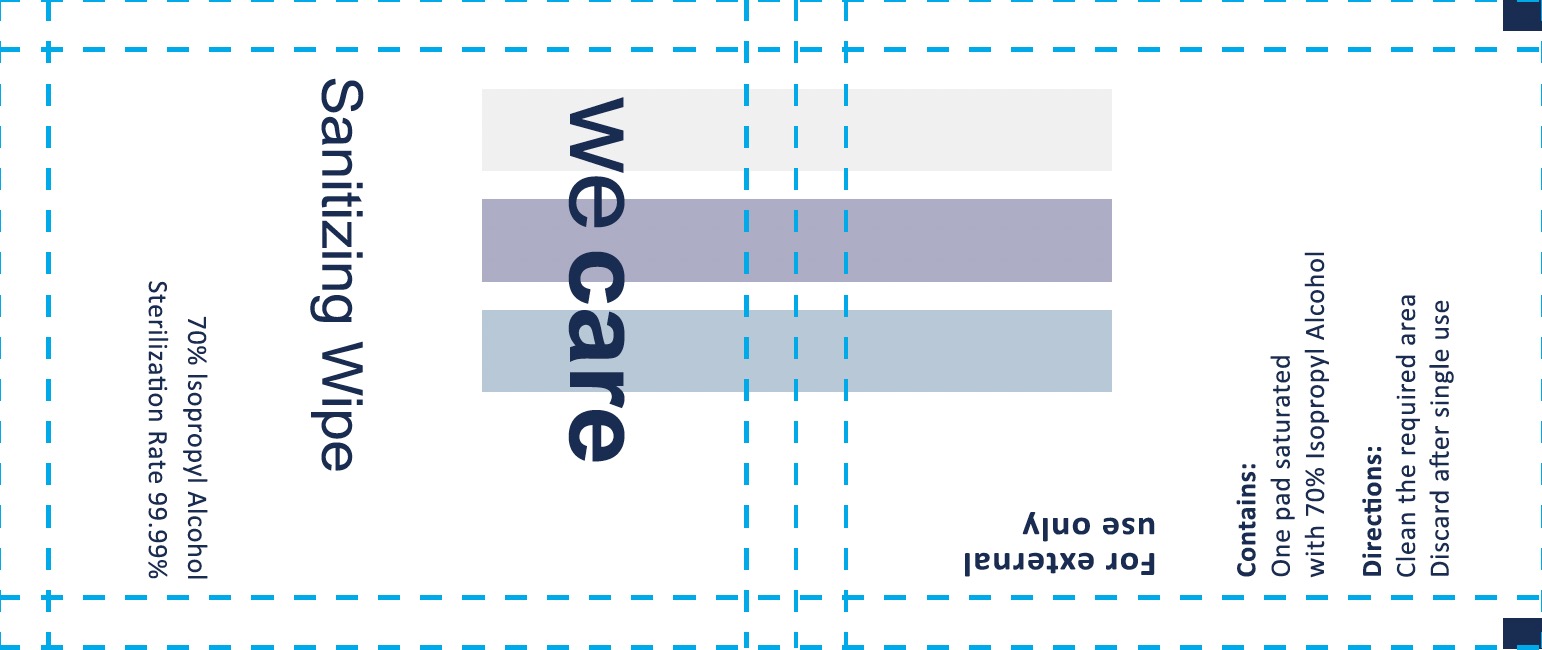 DRUG LABEL: We Care Sanitizing Wipe
NDC: 80436-007 | Form: CLOTH
Manufacturer: RMT Global Partners, LLC
Category: otc | Type: HUMAN OTC DRUG LABEL
Date: 20251221

ACTIVE INGREDIENTS: ISOPROPYL ALCOHOL 70 mL/100 mL
INACTIVE INGREDIENTS: WATER

RTM WeCare Sanitizing Wipe

Active Ingredient(s)

Isopropyl alcohol 70 %

Purpose

Antiseptic

Use

For hand sanitizing to decrease bacteria on the skin. Recommended for repeated use

Warnings

Warnings For external use only
When using this, avoid contact with the eyes. In case of eye contact, flush eyes with water.

Do not use in or near the eyes. In case of contact with eyes flush thoroughly with water.

Stop use and ask a doctor if irritation or redness develops, —
or if the condition persists for more than 72 hours.

Keep out of reach of children. If swallowed, get medical
help or contact a Poison Control Center right away.

Directions

Apply to hands, Allow skin to dry without wiping

Inactive ingredients

Water